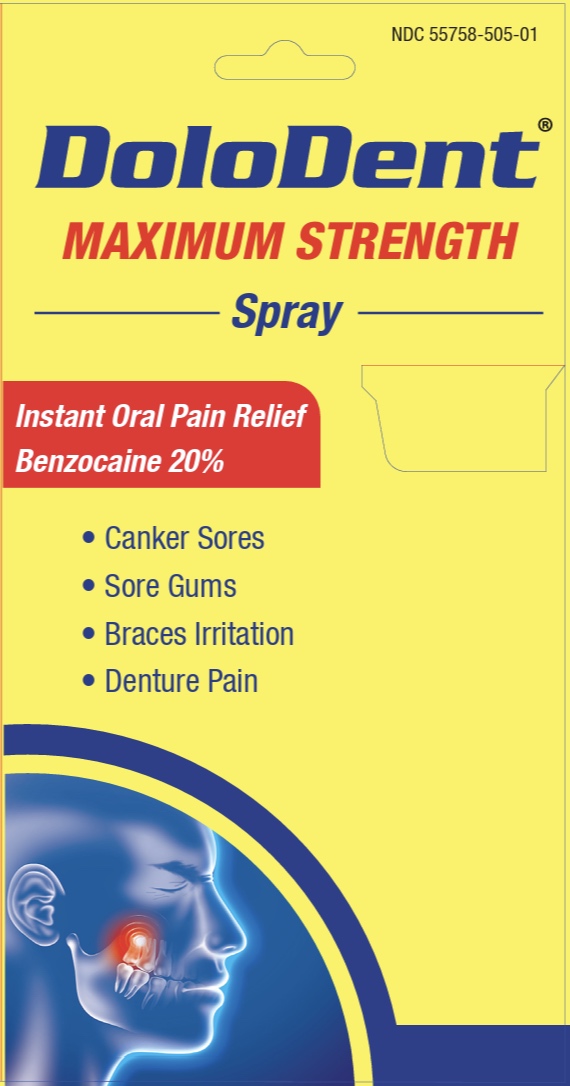 DRUG LABEL: Dolodent
NDC: 55758-505 | Form: LIQUID
Manufacturer: Pharmadel LLC
Category: otc | Type: HUMAN OTC DRUG LABEL
Date: 20251204

ACTIVE INGREDIENTS: BENZOCAINE 200 mg/1 mL
INACTIVE INGREDIENTS: ALCOHOL; CLOVE OIL; GLYCERIN; POLYETHYLENE GLYCOL, UNSPECIFIED; SODIUM SACCHARIN; SODIUM METHYLPARABEN; PROPYLENE GLYCOL

DoloDent (WP)(DA)

Active ingredient and Purpose

.

Active ingredient | Purpose
Benzocaine 20%...................... | Oral pain reliever

Uses

For the temporary relief of

- canker sores
- minor injury of the mouth and gums
- minor irritation of the mouth and gums caused by dentures or orthodontic appliances

Warnings

Methemoglobinemia warning: Use of this product may cause methemoglobinemia, a serious condition that must be treated promptly because it reduces the amount of oxygen carried in blood. This can occur even if you have used this product before. Stop use and seek immediate medical attention if you or a child in your care develops:

- pale, gray, or blue colored skin (cyanosis)
- headache
- rapid heart rate
- shortness of breath
- dizziness or lightheadedness
- fatigue or lack of energy

Allergy alert: do not use this product if you have a history of allergy to local anesthetics such as procaine, butacaine, benzocaine, or other “caine” anesthetics.

Flammable. Keep away from fire or flame. Avoid smoking during application.

Do not use

- more than directed
- for more than 7 days unless directed by a dentist or doctor
- for teething
- in children under 2 years of age

Stop use and ask your doctor or dentist if

- sore mouth symptoms do not improve in 7 days
- irritation, pain or redness persists or worsens
- swelling, rash or fever develops

Keep out of reach of children.

If more than used for pain is accidentally swallowed or an allergic reaction occurs, get medical help or contact a Poison Control Center right away.

Directions

- adults and children 2 years of age and older:
- apply product to a cotton swab or finger to the affected area. Allow to remain in place at least 1 minute and then spit out. Use up to 4 times daily or as directed by a dentist or doctor
- children under 12 years of age should be supervised in the use of the product
- children under 2 years of age: do not use

Other information

- do not use if clear seal over cap is torn, broken, or missing
- store between 68-77°F (20-25°C)

Inactive ingredients

alcohol, clove oil, glycerin, polyethylene glycol, propylene glycol, sodium saccharin, sodium methylparaben

Questions or comments?

+1-866-359-3478 (M-F) 9 AM to 5 PM EST or www.pharmadel.com

Dist. by/ por:

PHARMADEL LLC

New Castle, DE 19720

+1-866-359-3478

www.pharmadel.com